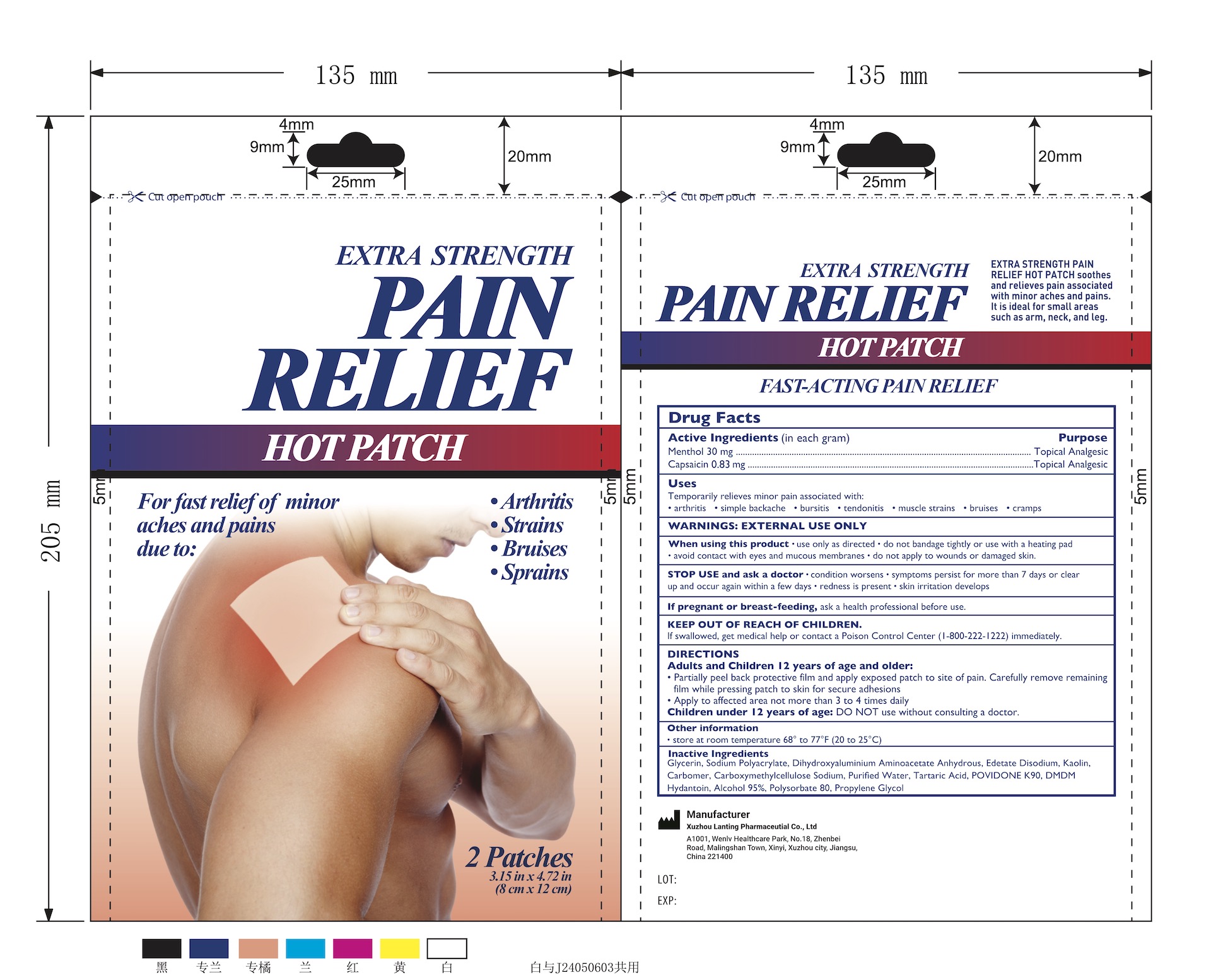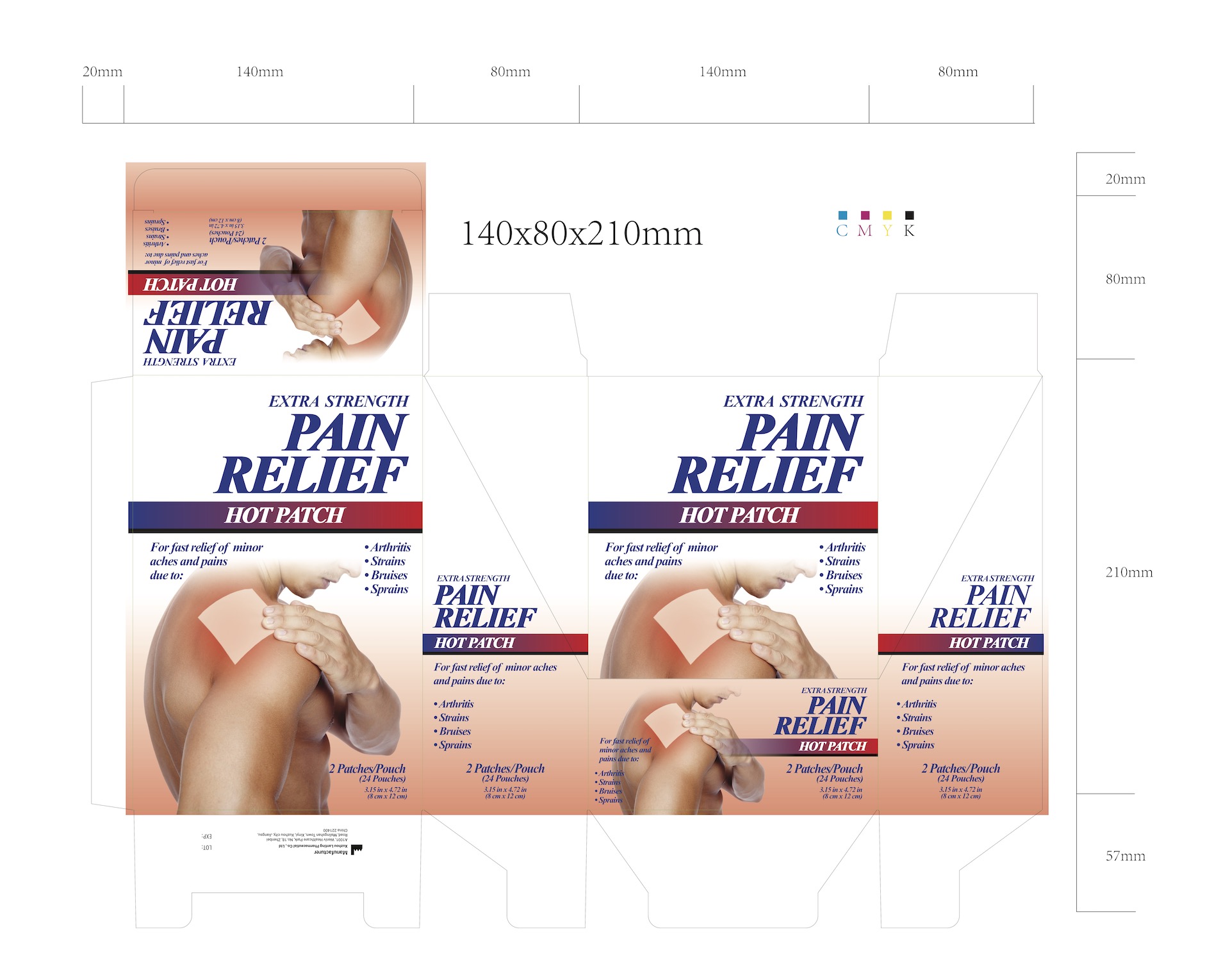 DRUG LABEL: 3% Menthol plus 0.083% Capsaicin Pain Relief Patch
NDC: 85323-008 | Form: PATCH
Manufacturer: Xuzhou Lanting Pharmaceutical Co., Ltd
Category: otc | Type: HUMAN OTC DRUG LABEL
Date: 20250610

ACTIVE INGREDIENTS: MENTHOL 3 g/100 g; CAPSAICIN 83 mg/100 g
INACTIVE INGREDIENTS: SODIUM POLYACRYLATE (2500000 MW); ALCOHOL 95%; WATER; DIHYDROXYALUMINUM AMINOACETATE ANHYDROUS; KAOLIN; PROPYLENE GLYCOL; EDETATE DISODIUM; CARBOMER 934; TARTARIC ACID; POLYSORBATE 80; POVIDONE K90; GLYCERIN; CARBOXYMETHYLCELLULOSE SODIUM; DMDM HYDANTOIN

85323-008, 3% Menthol plus 0.083% Capsaicin Pain Relief Patch

3% Menthol plus 0.083% Capsaicin Pain Relief Patch, Package NDC Code: 85323-008-01

Active Ingredient

Active Ingredients (in each gram):

Menthol 30mg

Capsaicin 0.83mg

Purpose

Purpose: Topical anesthetic

Uses

Temporarily relieves minor pain associated with:

- arthritis
- simple backache
- bursitis
- tendonitis
- muscle strains
- bruises
- cramps

Warnings

WARNINGS: EXTERNAL USE ONLY

When using this product

- use only as directed
- do not bandage tightly or use with a heating pad
- aviod contact with eyes and mucous membranes
- do not apply to wounds or damaged skin

Stop use and ask a doctor

- condition worsens
- symptoms persist for more than 7 days or clear up and occur again within a few days
- redness is present
- skin irritation develops

If pregnant or breast-feeding, ask a health professional before use.

KEEP OUT OF REACH OF CHILDREN.

If swallowed, get medical help or contact a Poison Control Center (1-800-222-1222) immediately.

Other information

- store at room temperature 68 to 77℉ (20-25℃)

Inactive Ingredients

Glycerin, Sodium Polyacrylate, Dihydroxyaluminum Aminoacetate Anhydrous, Edetate Disodium, Kaolin, Carbomer, Carboxymethylcellulose Sodium, Purified Water, Tartaric Acid, Povidone K90, DMDM Hydantoin, Alcohol 95%, Polysorbate 80, Propylene Glycol.

KEEP OUT OF REACH OF CHILDREN.

If swallowed, get medical help or contact a Poison Control Center (1-800-222-1222) immediately.

Directions

Adult and children 12 years of age and older:

- Partially peel back protective film and apply exposed patch to site of pain. Carefully remove remaining film while pressing patch to skin for secure adhesions
- Apply to affected area not more than 3 to 4 times daily

Children under 12 years of age: DO NOT use without consulting a doctor.

INDICATIONS AND USAGE

Temporarily relieves minor pain associated with:

- arthritis
- simple backache
- bursitis
- tendonitis
- muscle strains
- bruises
- cramps

Adult and children 12 years of age and older:

- Partially peel back protective film and apply exposed patch to site of pain. Carefully remove remaining film while pressing patch to skin for secure adhesions
- Apply to affected area not more than 3 to 4 times daily

Children under 12 years of age: DO NOT use without consulting a doctor.